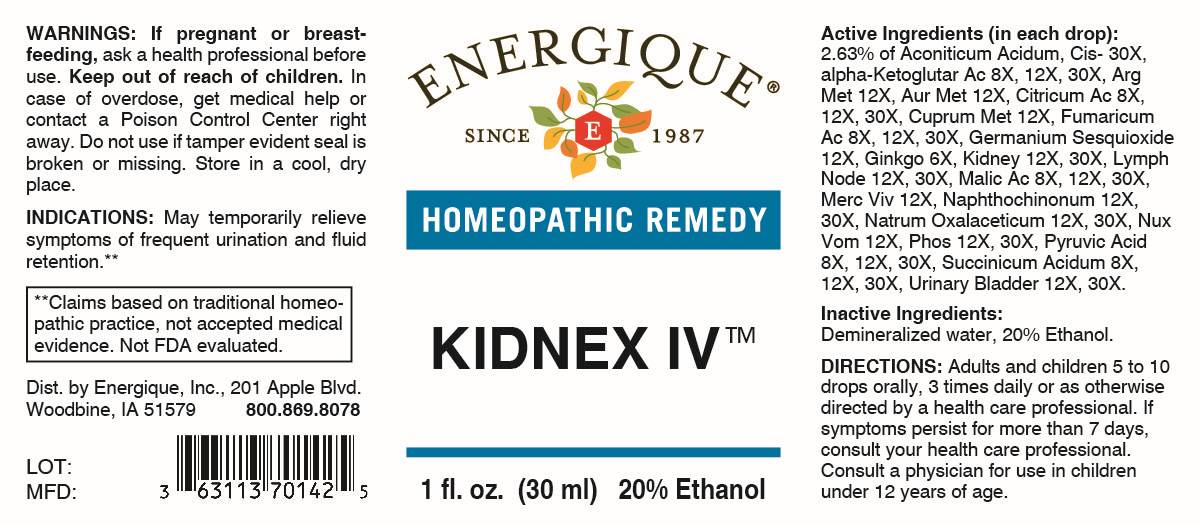 DRUG LABEL: Kidnex IV
NDC: 44911-0747 | Form: LIQUID
Manufacturer: Energique, Inc.
Category: homeopathic | Type: HUMAN OTC DRUG LABEL
Date: 20260226

ACTIVE INGREDIENTS: GINKGO 6 [hp_X]/1 mL; OXOGLURIC ACID 8 [hp_X]/1 mL; ANHYDROUS CITRIC ACID 8 [hp_X]/1 mL; FUMARIC ACID 8 [hp_X]/1 mL; MALIC ACID 8 [hp_X]/1 mL; PYRUVIC ACID 8 [hp_X]/1 mL; SUCCINIC ACID 8 [hp_X]/1 mL; SILVER 12 [hp_X]/1 mL; GOLD 12 [hp_X]/1 mL; COPPER 12 [hp_X]/1 mL; GERMANIUM SESQUIOXIDE 12 [hp_X]/1 mL; MERCURY 12 [hp_X]/1 mL; STRYCHNOS NUX-VOMICA SEED 12 [hp_X]/1 mL; PORK KIDNEY 12 [hp_X]/1 mL; SUS SCROFA LYMPH 12 [hp_X]/1 mL; 1,4-NAPHTHOQUINONE 12 [hp_X]/1 mL; SODIUM DIETHYL OXALACETATE 12 [hp_X]/1 mL; PHOSPHORUS 12 [hp_X]/1 mL; SUS SCROFA URINARY BLADDER 12 [hp_X]/1 mL; ACONITIC ACID, (Z)- 30 [hp_X]/1 mL
INACTIVE INGREDIENTS: WATER; ALCOHOL

DRUG FACTS:

ACTIVE INGREDIENTS:

(in each drop): 2.63% of Aconiticum Acidum, Cis- 30X, Alpha-Ketoglutaricum Acidum 8X, 12X, 30X, Argentum Metallicum 12X, Aurum Metallicum 12X, Citricum Acidum 8X, 12X, 30X, Cuprum Metallicum 12X, Fumaricum Acidum 8X, 12X, 30X, Germanium Sesquioxide 12X, Ginkgo Biloba 6X, Kidney 12X, 30X, Lymph Node 12X, 30X, Malicum Acidum 8X, 12X, 30X, Mercurius Vivus 12X, Naphthochinonum 12X, 30X, Natrum Oxalaceticum 12X, 30X, Nux Vomica 12X, Phosphorus 12X, 30X, Pyruvic Acid 8X, 12X, 30X, Succinicum Acidum 8X, 12X, 30X, Urinary Bladder 12X, 30X.

PURPOSE:

May temporarily relieve symptoms of frequent urination and fluid retention.**

**Claims based on traditional homeopathic practice, not accepted medical evidence, Not FDA evaluated.

WARNINGS:

If pregnant or breast-feeding, ask a health professional before use.

Keep out of reach of children. In case of overdose, get medical help or contact a Poison Control Center right away.

Do not use if tamper evident seal is broken or missing. Store in a cool, dry place.

KEEP OUT OF REACH OF CHILDREN:

In case of overdose, get medical help or contact a Poison Control Center right away.

DIRECTIONS:

Adults and children 5 to 10 drops orally, 3 times daily or as otherwise directed by a health care professional. If symptoms persist for more than 7 days, consult your health care professional. Consult a physician for use in children under 12 years of age.

USES:

May temporarily relieve symptoms of frequent urination and fluid retention.**

**Claims based on traditional homeopathic practice, not accepted medical evidence, Not FDA evaluated.

INACTIVE INGREDIENTS:

Demineralized water, 20% Ethanol.

QUESTIONS:

Dist. by Energique, Inc.

201 Apple Blvd

Woodbine, IA 51579

800.869.8078

PACKAGE LABEL DISPLAY:

ENERGIQUE

SINCE 1987

HOMEOPATHIC REMEDY

KIDNEX IV

1 fl. oz. (30 ml)